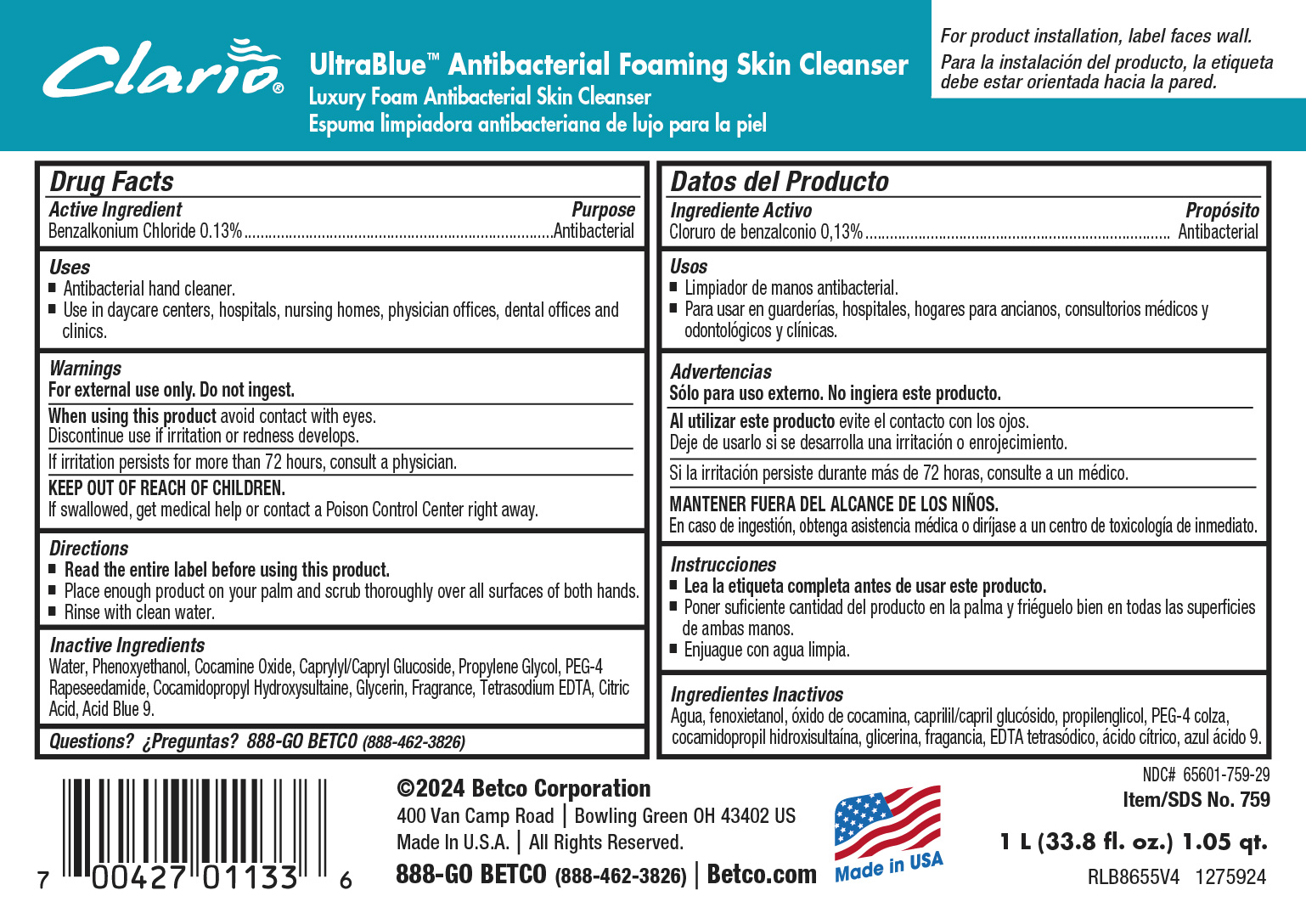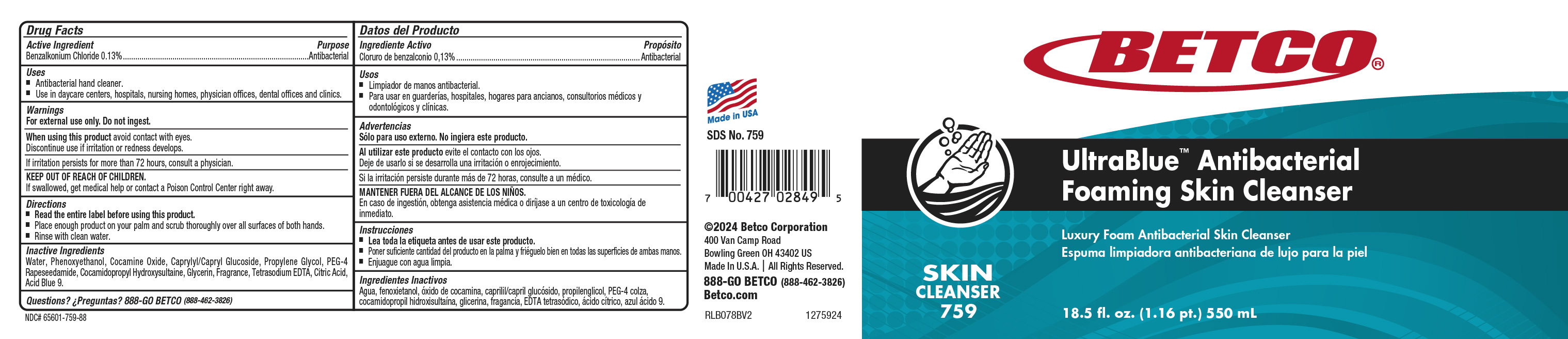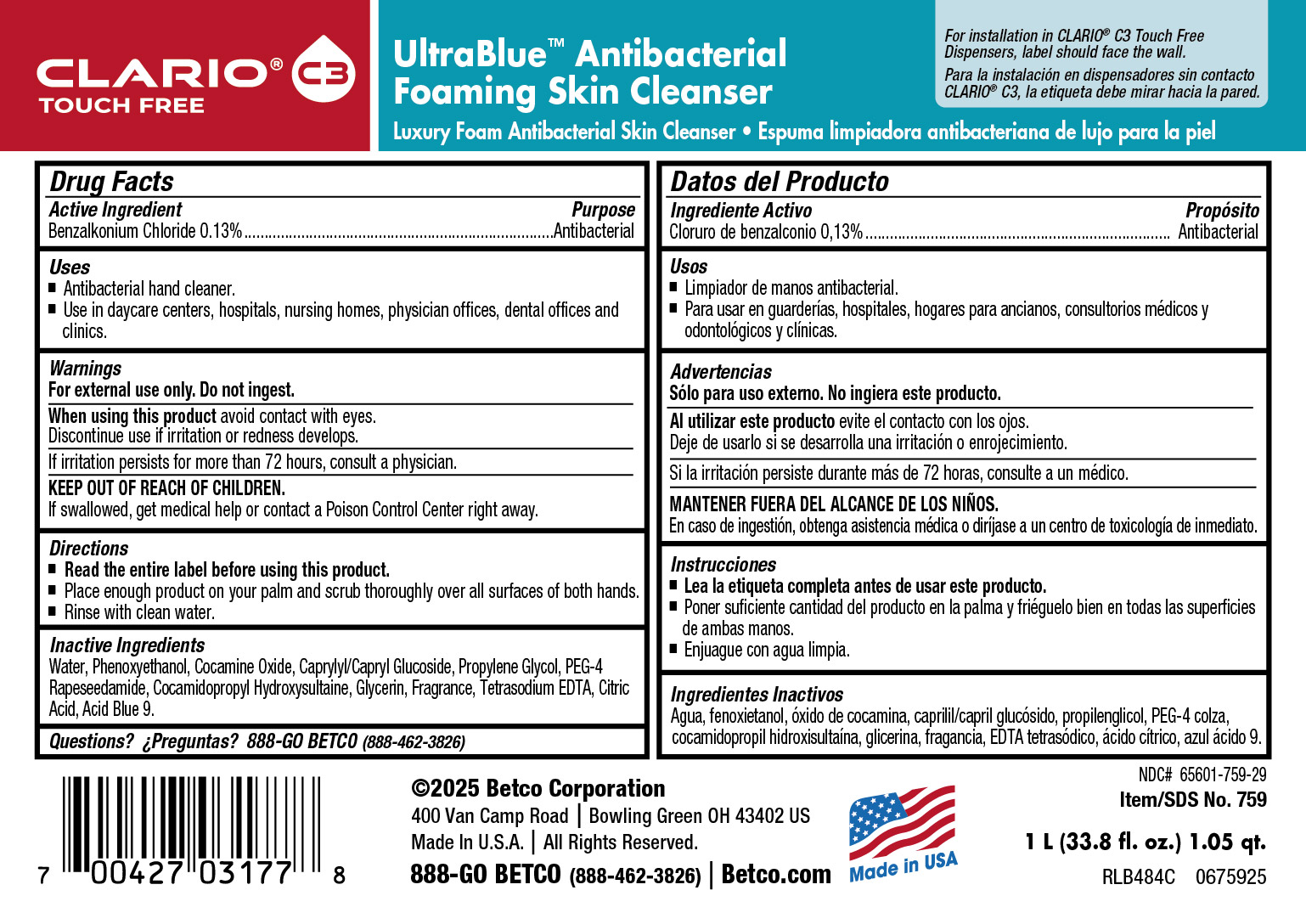 DRUG LABEL: Ultra Blue Antibacterial Foaming Skin Cleanser
NDC: 65601-759 | Form: SOAP
Manufacturer: Betco Corporation, Ltd
Category: otc | Type: HUMAN OTC DRUG LABEL
Date: 20260218

ACTIVE INGREDIENTS: BENZALKONIUM CHLORIDE 1.3 mg/1 mL
INACTIVE INGREDIENTS: SODIUM GLYCOLATE; SODIUM HYDROXIDE; TRISODIUM NITRILOTRIACETATE; FD&C BLUE NO. 1; N-ALKYL DIMETHYL BENZYL AMMONIUM CHLORIDE (C12-C18); ANHYDROUS CITRIC ACID; 2,4-DIMETHYL-3-CYCLOHEXENE CARBOXALDEHYDE; METHYL DIHYDROJASMONATE (SYNTHETIC); CAPRYLYL/CAPRYL OLIGOGLUCOSIDE; MAGNESIUM NITRATE; METHYLCHLOROISOTHIAZOLINONE; GERANIOL; LIME OIL; 2-METHYLUNDECANAL; .BETA.-CITRONELLOL, (+/-)-; ALLYL CYCLOHEXANEPROPIONATE; GERANYL ACETATE; CITRONELLYL ACETATE; LINALOOL, (+/-)-; METHYLISOTHIAZOLINONE; CITRAL; FORMALDEHYDE; WATER; COCAMINE OXIDE; PROPYLENE GLYCOL; PEG-4 RAPESEEDAMIDE; COCAMIDOPROPYL HYDROXYSULTAINE; GLYCERIN; SODIUM CHLORIDE; EDETATE SODIUM; ALCOHOL; BENZYL ACETATE

UltraBlue™ Antibacterial Foaming Skin Cleanser

Active Ingredient

Benzalkonium Chloride 0.13%

Purpose

Antibacterial

Warnings

- For external use only. Do not ingest.
- Avoid contact with eyes. If contact occurs, rinse thoroughly with water.
- Stop use and ask a doctor if irritation and redness develop.
- If irritation persists for more than 72 hours, consult a physician.
- KEEP OUT OF REACH OF CHILDREN.
- If swallowed, get medical help or contact a Poison Control Center right away.

Directions

- ?Read the entire label before using this product.
- ?Dispense 2 pumps of product onto palm of hand and scrub thoroughly over all surfaces of both hands.
- Rinse with clean water.

Inactive Ingredients

Water, Phenoxyethanol, Cocamine Oxide, Propylene Glycol, Decyl Glucoside, PEG-4 Rapeseedamide, Cocamidopropyl Hydroxysultaine, Glycerin, Fragrance, Sodium Chloride, Tetrasodium EDTA, Citric Acid, Ethanol, Iodopropynyl Butylcarbamate, Benzyl Acetate, Sodium Glycolate, Sodium Hydroxide, Trisodium Nitrilotriacetate, Diethyl Phthalate, FD&C Blue #1.

Questions? 888-GO BETCO (888-462-3826)

Clario Ultra Blue Antibacterial Foaming Skin Cleanser

Purpose

Antibacterial

Clario Ultra Blue Antibacterial Foaming Skin Cleanser

KEEP OUT OF REACH OF CHILDREN